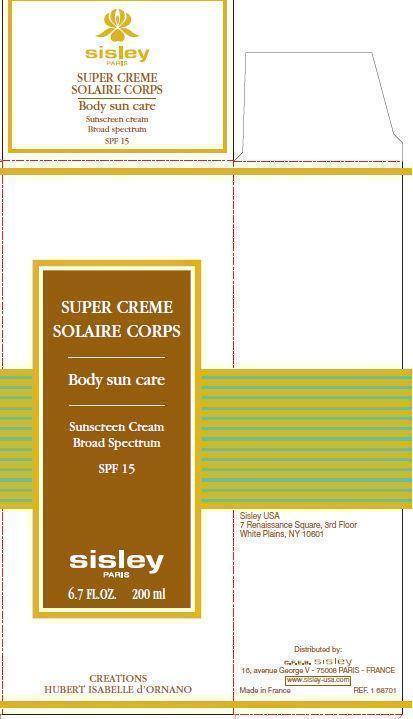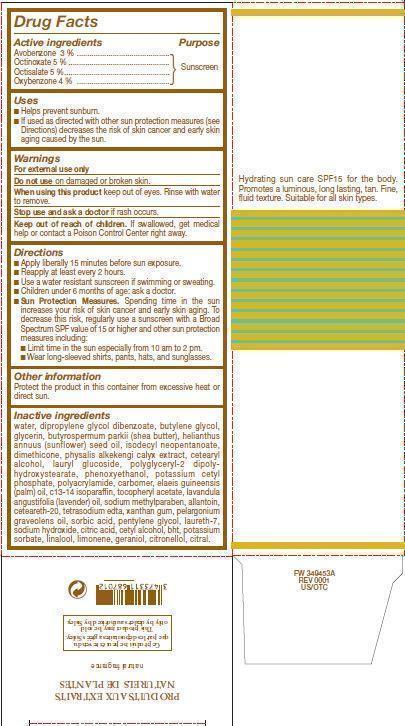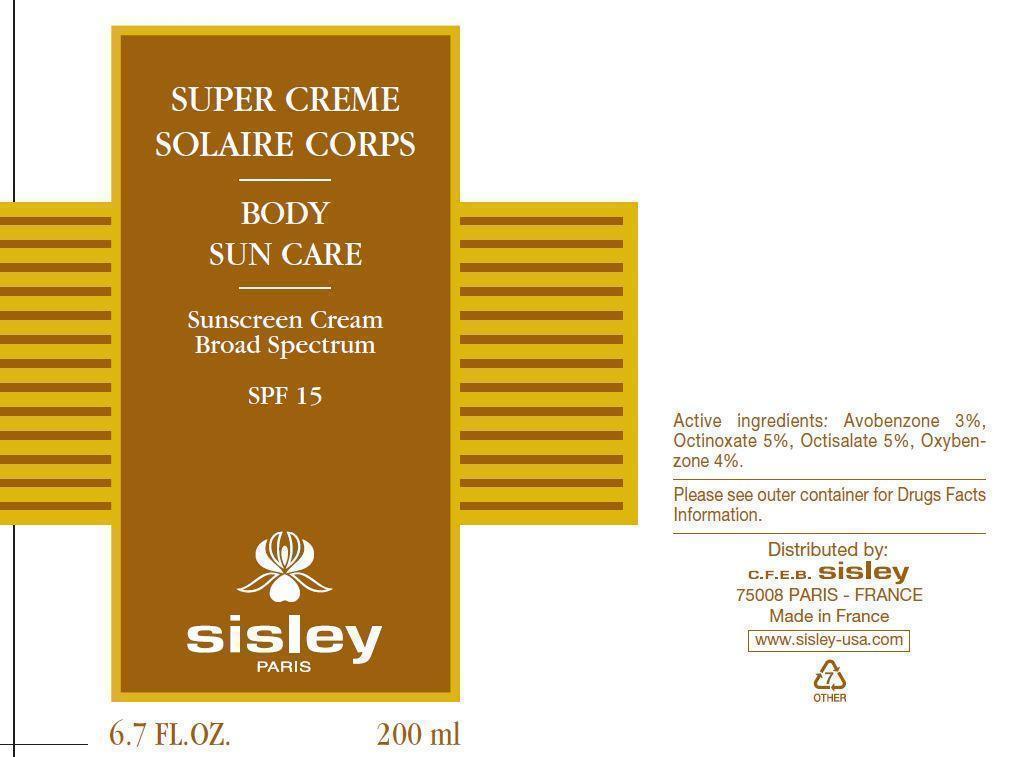 DRUG LABEL: 
                  SUPER CREME SOLAIRE CORPS Body sun care

                
                  

NDC: 66097-004 | Form: CREAM
Manufacturer: C.F.E.B. Sisley
Category: otc | Type: HUMAN OTC DRUG LABEL
Date: 20241210

ACTIVE INGREDIENTS: AVOBENZONE 30 mg/1 mL; OCTINOXATE 50 mg/1 mL; OCTISALATE 50 mg/1 mL; OXYBENZONE 40 mg/1 mL
INACTIVE INGREDIENTS: WATER; DIPROPYLENE GLYCOL DIBENZOATE; BUTYLENE GLYCOL; GLYCERIN; SHEANUT OIL; SUNFLOWER OIL; ISODECYL NEOPENTANOATE; DIMETHICONE; PHYSALIS ALKEKENGI CALYX; CETOSTEARYL ALCOHOL; LAURYL GLUCOSIDE; POLYGLYCERYL-2 DIPOLYHYDROXYSTEARATE; PHENOXYETHANOL; POTASSIUM CETYL PHOSPHATE; PALM OIL; C13-14 ISOPARAFFIN; .ALPHA.-TOCOPHEROL ACETATE; LAVENDER OIL; METHYLPARABEN SODIUM; ALLANTOIN; POLYOXYL 20 CETOSTEARYL ETHER; EDETATE SODIUM; XANTHAN GUM; GERANIUM OIL, ALGERIAN TYPE; SORBIC ACID; PENTYLENE GLYCOL; LAURETH-7; SODIUM HYDROXIDE; CITRIC ACID MONOHYDRATE; CETYL ALCOHOL; BUTYLATED HYDROXYTOLUENE; POTASSIUM SORBATE; LINALOOL, (+/-)-; GERANIOL; .BETA.-CITRONELLOL, (R)-; CITRAL

SUPER CREME SOLAIRE CORPS Body sun care SPF 15

Active ingredients

Avobenzone 3 % Octinoxate 5 % Octisalate 5 % Oxybenzone 4 %

Purpose

Sunscreen

Uses

- Helps prevent sunburn
- If used as directed with other sun protection measures (see Directions) decreases the risk of skin cancer and early skin aging caused by the sun.

Warnings

For external use only

Do not use

on damaged or broken skin.

When using this product

keep out of eyes. Rinse with water to remove.

Stop use and ask a doctor

if rash occurs.

Keep out of reach of children.

If swallowed, get medical help or contact a Poison Control Center right away.

Directions

- Apply liberally 15 minutes before sun exposure.
- Reapply at least every 2 hours.
- Use a water resistant sunscreen if swimming or sweating.
- Children under 6 months of age: ask a doctor.
- Spending time in the sun increases your risk of skin cancer and early skin aging. To decrease this risk, regularly use a sunscreen with a Broad Spectrum SPF value of 15 or higher and other sun protection measures including: Sun Protection Measures:
- Limit time in the sun especially from 10 am to 2 pm.
- Wear long-sleeved shirts, pants, hats, and sunglasses.

Other information

Protect the product in this container from excessive heat or direct sun.

Inactive ingredients

water, dipropylene glycol dibenzoate, butylene glycol, glycerin, butyrospermum parkii (shea butter), helianthus annuus (sunflower) seed oil, isodecyl neopentanoate, dimethicone, physalis alkekengi calyx extract, cetearyl alcohol, lauryl glucoside, polyglyceryl-2 dipolyhydroxystearate, phenoxyethanol, potassium cetyl phosphate, polyacrylamide, carbomer, elaeis guineensis (palm) oil, c13-14 isoparaffin, tocopheryl acetate, lavandula angustifolia (lavender) oil, sodium methyl paraben, allantoin, ceteareth-20, tetrasodium edta, pelargonium graveolens oil, sorbic acid, pentylene glycol, laureth-7, sodium hydroxide, citric acid, cetyl alcohol, bht, potassium sorbate, linalool, limonene, geraniol, citronellol, citral

PACKAGE LABEL

SUPER CREME SOLAIRE CORPS Body sun care Sunscreen Cream Broad Spectrum SPF 15 sisley PARIS 6.7 FL.OZ. 200 ml Sisley USA 7 Renaissance Square, 3rd Floor, White Plains, NY 10601